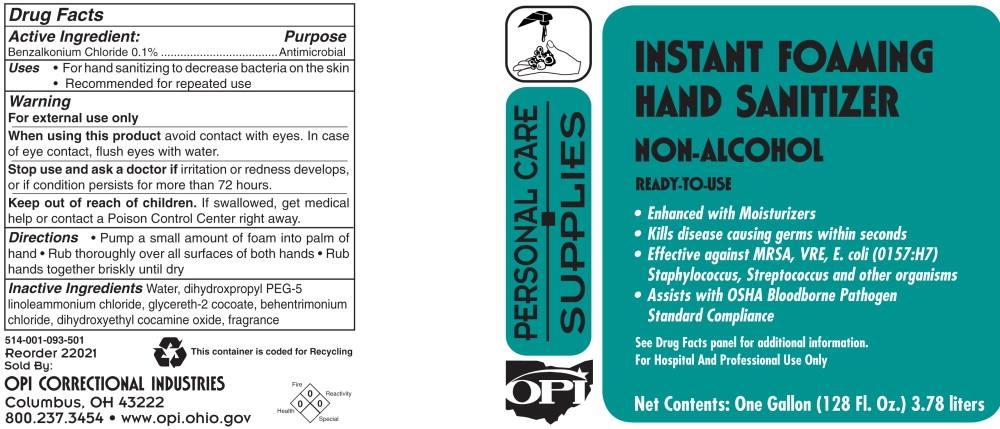 DRUG LABEL: OPI Personal Care Supplies Instant Foaming Hand Sanitizer Non Alcohol
NDC: 43196-514 | Form: SOLUTION
Manufacturer: OPI Correctional Industries
Category: otc | Type: HUMAN OTC DRUG LABEL
Date: 20100308

ACTIVE INGREDIENTS: benzalkonium chloride 1 g/1000 mL
INACTIVE INGREDIENTS: water; dihydroxypropyl peg-5 linoleammonium chloride; glycereth-2 cocoate; behentrimonium chloride; dihydroxyethyl cocamine oxide

Instant Foaming Hand Sanitizer Non Alcohol

Active Ingredient

Benzalkonium Chloride 0.1%

Purpose

Antimicrobial

Uses

- For hand sanitizing to decrease bacteria on the skin
- Recommended for repeated use

Warning

For external use only

When using this product avoid contact with eyes. In case of eye contact, flush eyes with water.

Stop use and ask a doctor if irritation or redness develops, or if condition persists for more than 72 hours.

Keep out of reach of children. If swallowed, get medical help or contact a Poison Control Center right away.

Directions

- Pump a small amount of foam into palm of hand
- Rub thoroughly over all surfaces of both hands
- Rub hands together briskly until dry

Inactive Ingredients

Water, dihydroxpropyl PEG-5 linoleammonium chloride, glycereth-2 cocoate, behentrimonium chloride, dihydroxyethyl cocamine oxide, fragrance

Principal Display Panel

OPI Personal Care Supplies

Instant Foaming Hand Sanitizer Non Alcohol

Ready-to-Use

- Enhanced with Moisturizers
- Kills disease causing germs within seconds
- Effective against MRSA, VRE, E. coli (0157:H7) Staphylococcus, Streptococcus and other organisms
- Assists with OSHA Bloodborne Pathogen Standard Compliance

See Drug Facts panel for additional information.

For Hospital and Professional Use Only